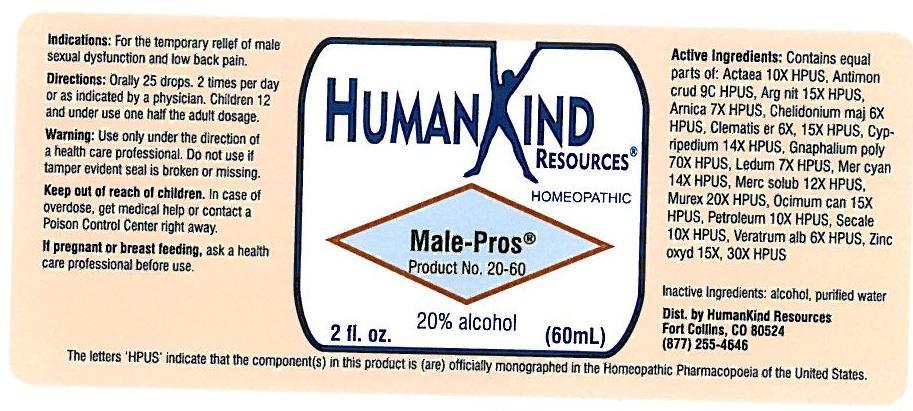 DRUG LABEL: MALE-PROS
NDC: 64616-098 | Form: LIQUID
Manufacturer: Vitality Works, Inc.
Category: homeopathic | Type: HUMAN OTC DRUG LABEL
Date: 20251217

ACTIVE INGREDIENTS: ANTIMONY TRISULFIDE 9 [hp_C]/1 mL; SILVER NITRATE 15 [hp_X]/1 mL; ARNICA MONTANA 7 [hp_X]/1 mL; CHELIDONIUM MAJUS 6 [hp_X]/1 mL; CLEMATIS RECTA FLOWERING TOP 15 [hp_X]/1 mL; CYPRIPEDIUM PARVIFLORUM VAR. PUBESCENS ROOT 14 [hp_X]/1 mL; PSEUDOGNAPHALIUM OBTUSIFOLIUM 70 [hp_X]/1 mL; LEDUM PALUSTRE TWIG 7 [hp_X]/1 mL; MERCURIC CYANIDE 14 [hp_X]/1 mL; MERCURIUS SOLUBILIS 12 [hp_X]/1 mL; HEXAPLEX TRUNCULUS HYPOBRANCHIAL GLAND JUICE 20 [hp_X]/1 mL; OCIMUM AMERICANUM LEAF 15 [hp_X]/1 mL; KEROSENE 10 [hp_X]/1 mL; VERATRUM ALBUM ROOT 6 [hp_X]/1 mL; ZINC OXIDE 6 [hp_X]/1 mL; ACTAEA SPICATA ROOT 10 [hp_X]/1 mL
INACTIVE INGREDIENTS: ALCOHOL; WATER

Male-Pros

MALE-PROS

Actaea Spicata 8X Ledum Palustre 7X

Antimonium Crudum 9C Mecurius Cyanatus 14X

Argentum Nitricum 13X Mercurius Solubilis 12X

Arnica Montana 5X Murex Purpurea 20X

Chelidonium Majus 6X Ocimum Canum 15X

Clematis Erecta 6X, 15X Petroleum 10X

Cypripedium Pubescens 14X Veratrum Album 6X

Gnaphalium Polycephalum 70X Zincum Oxydatum 15X, 30X

MALE-PROS

Alcohol, Purified Water

MALE-PROS

Use only under the direction of a health care professional. Do not use if tamper evident seal is broken or missing.

MALE-PROS

Keep out of reach of children. In case of overdose, get medical help or contact a Poison Control Center right away.

MALE-PROS

For the temporary relief of male sexual dysfunction and low back pain.

MALE-PROS

Orally 25 drops, 2 times per day or as indicated by a physician. Children 12 and under use one half the adult dosage.

MALE-PROS

Aids in prostrate health.